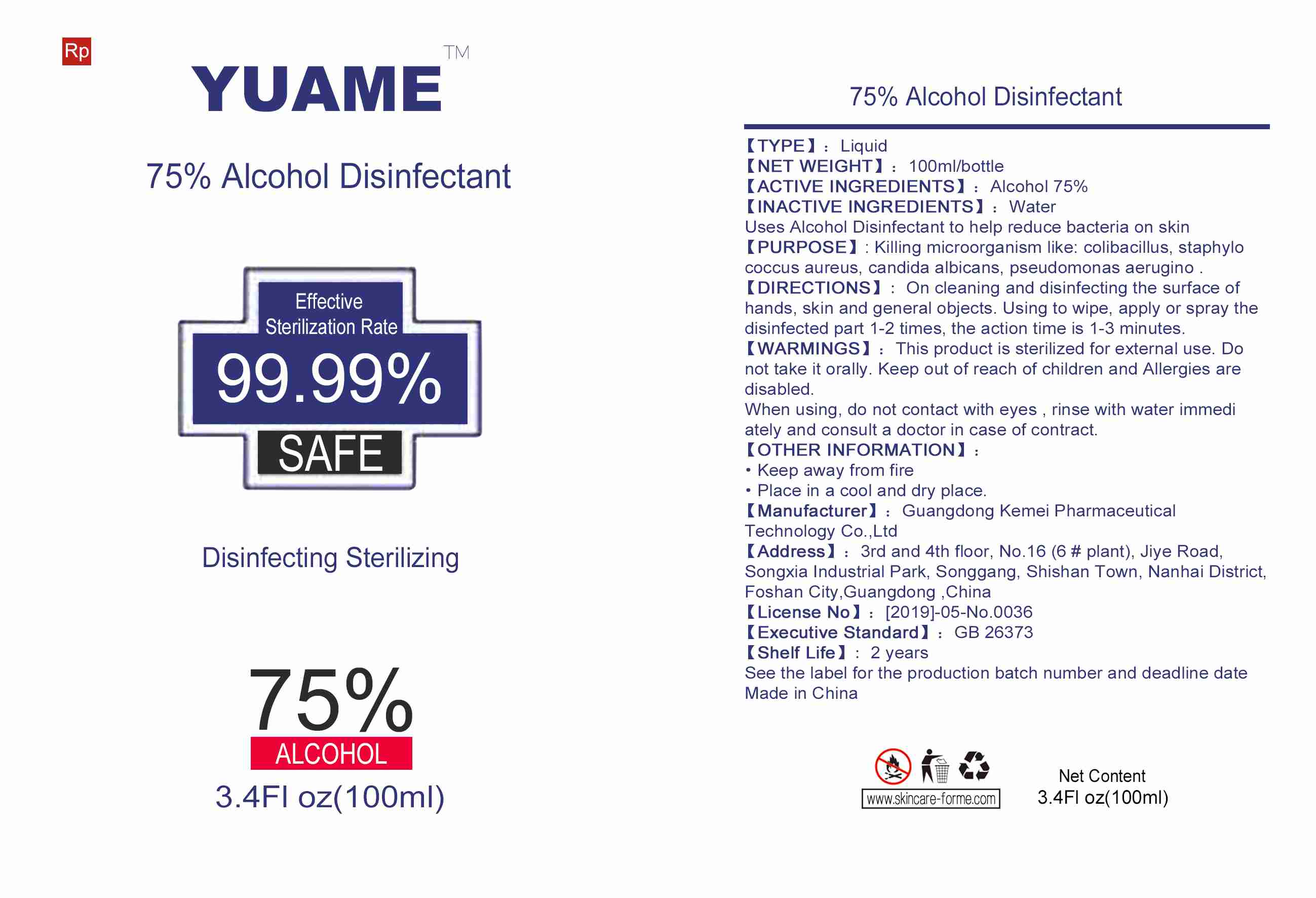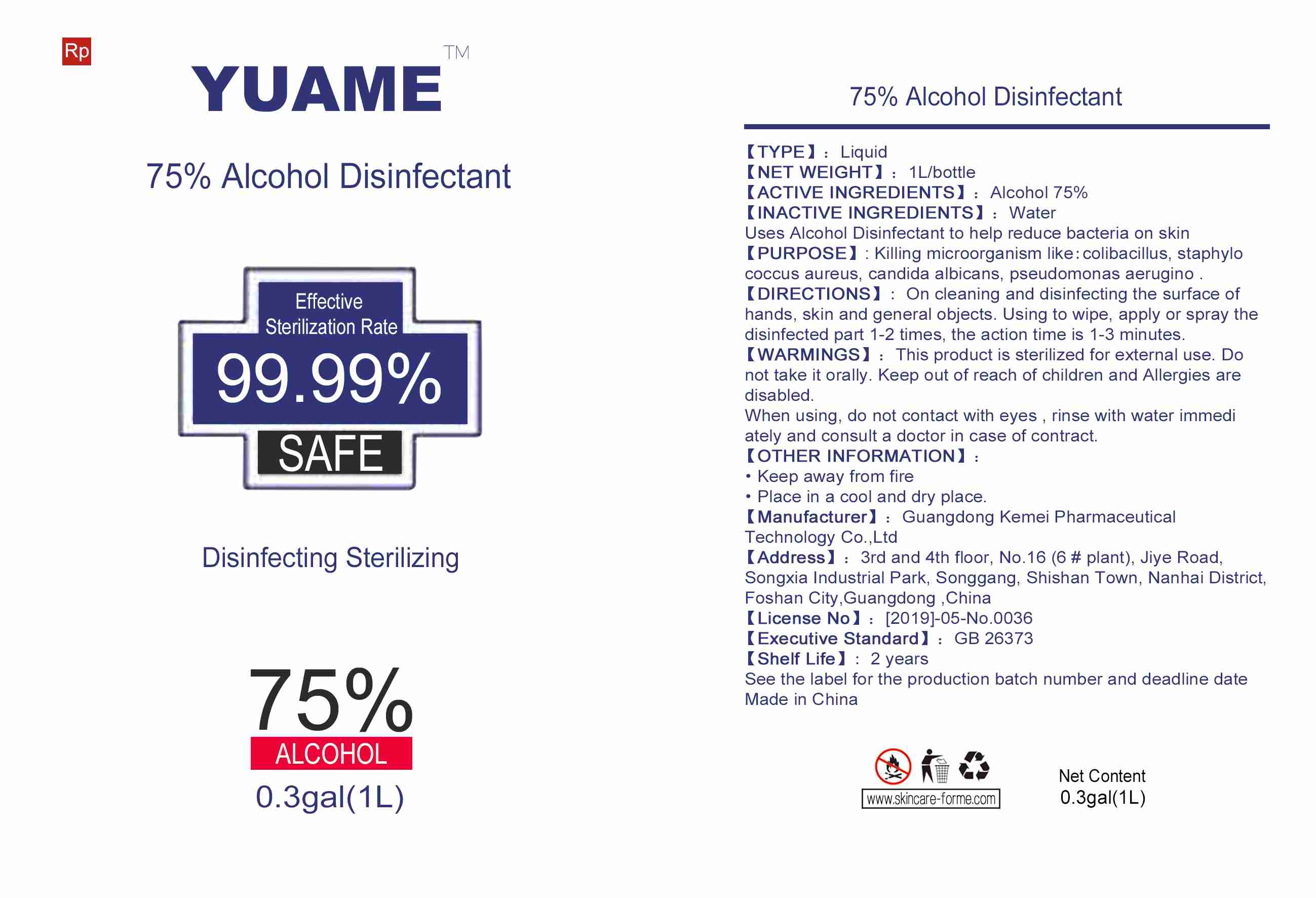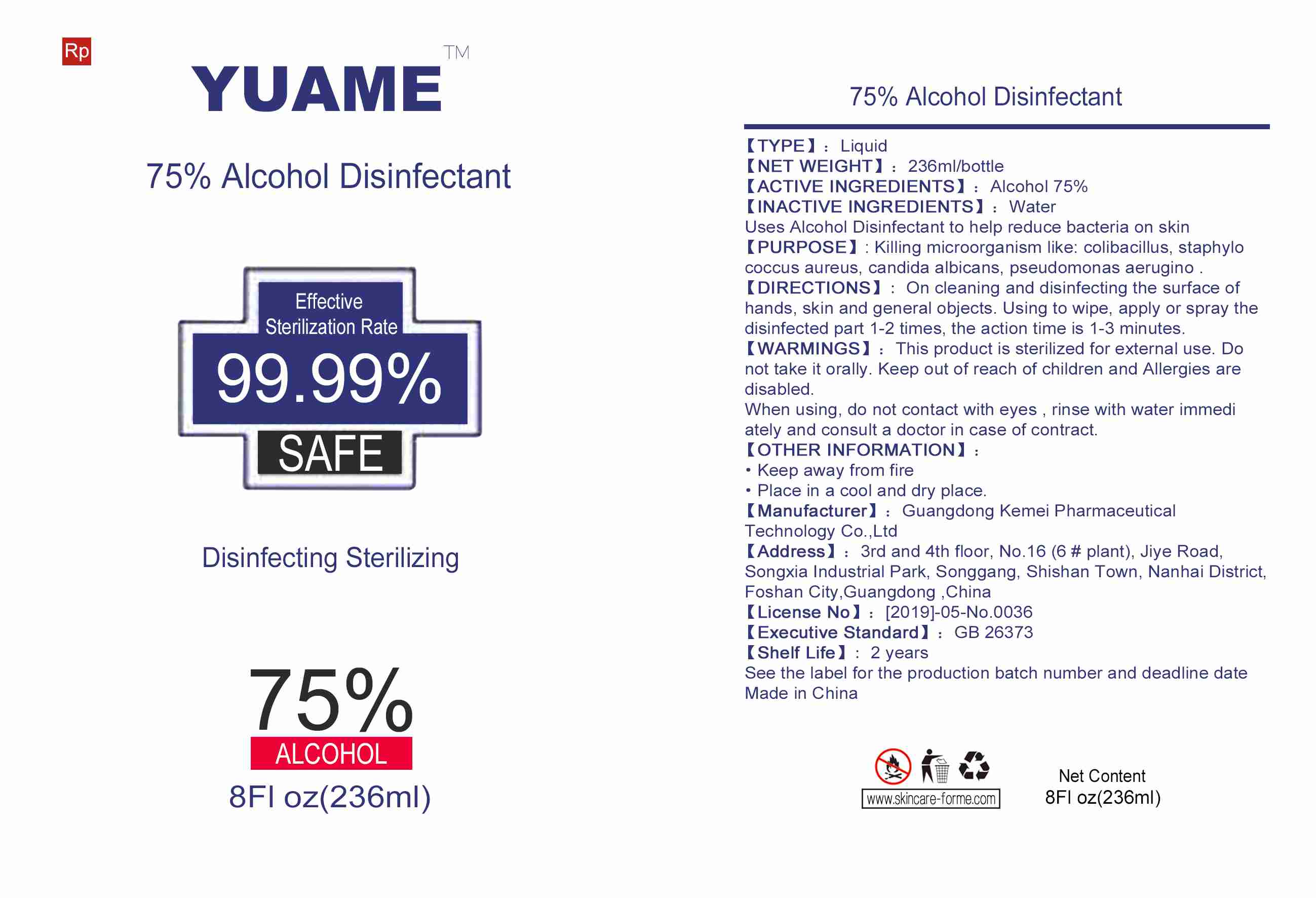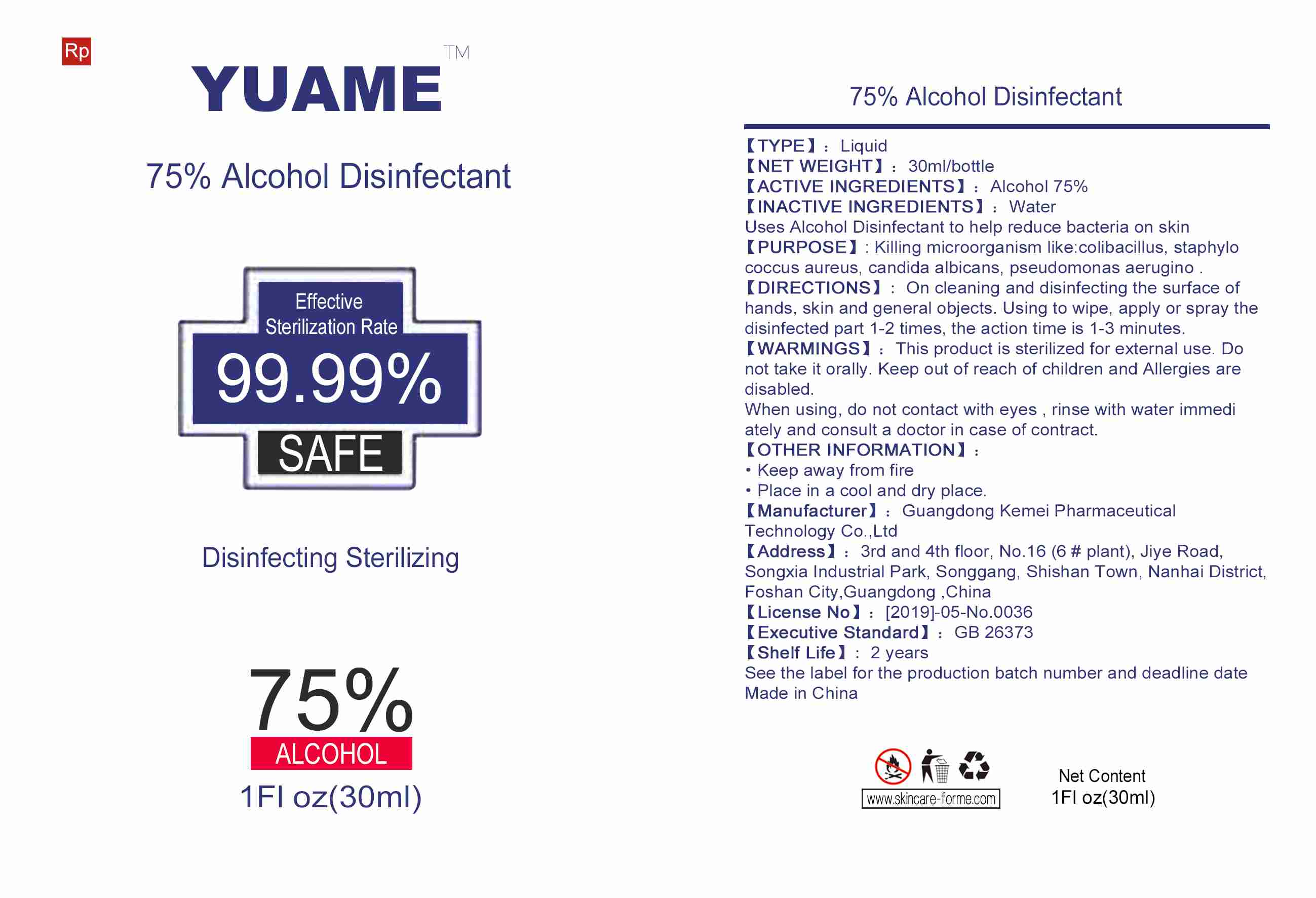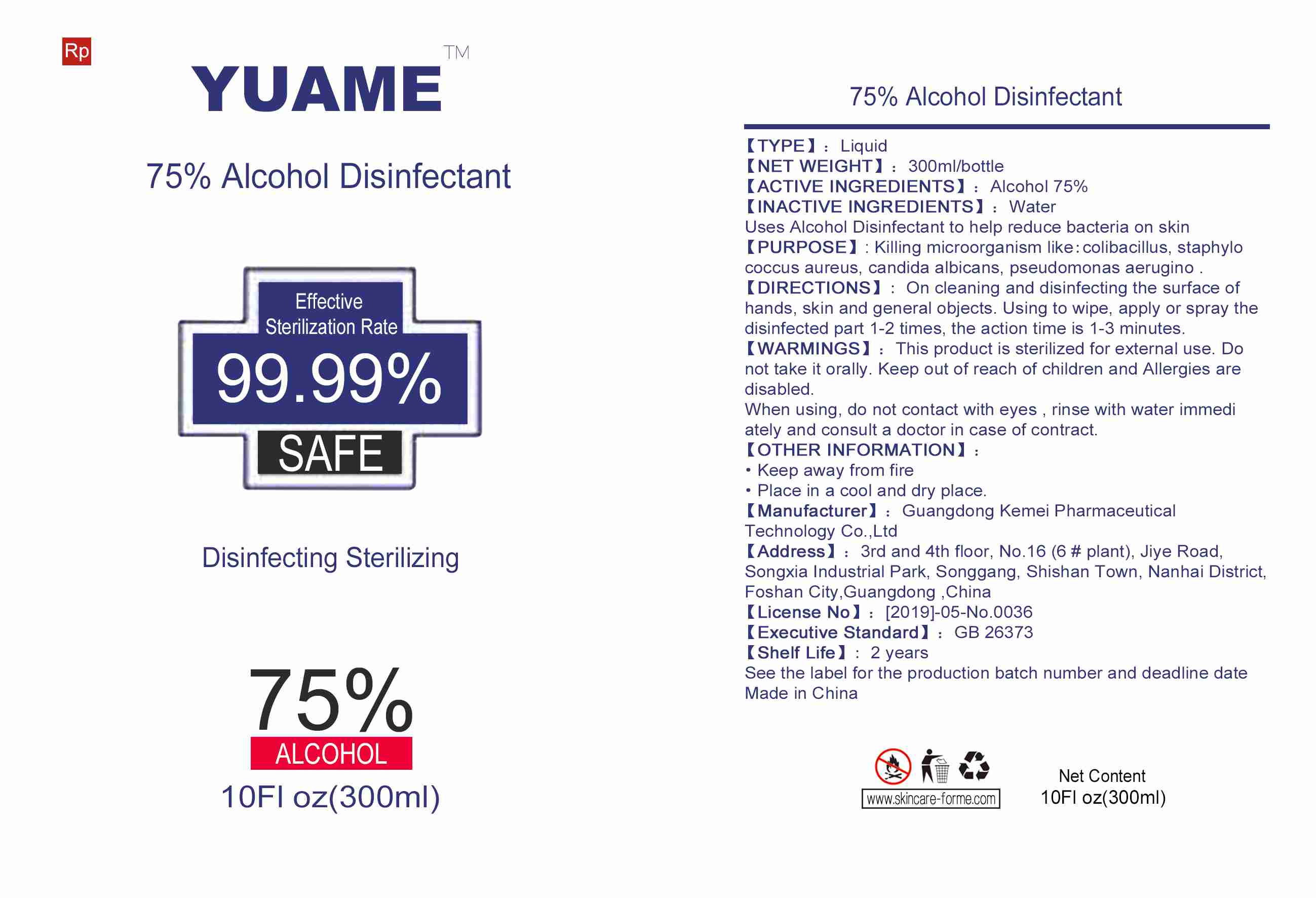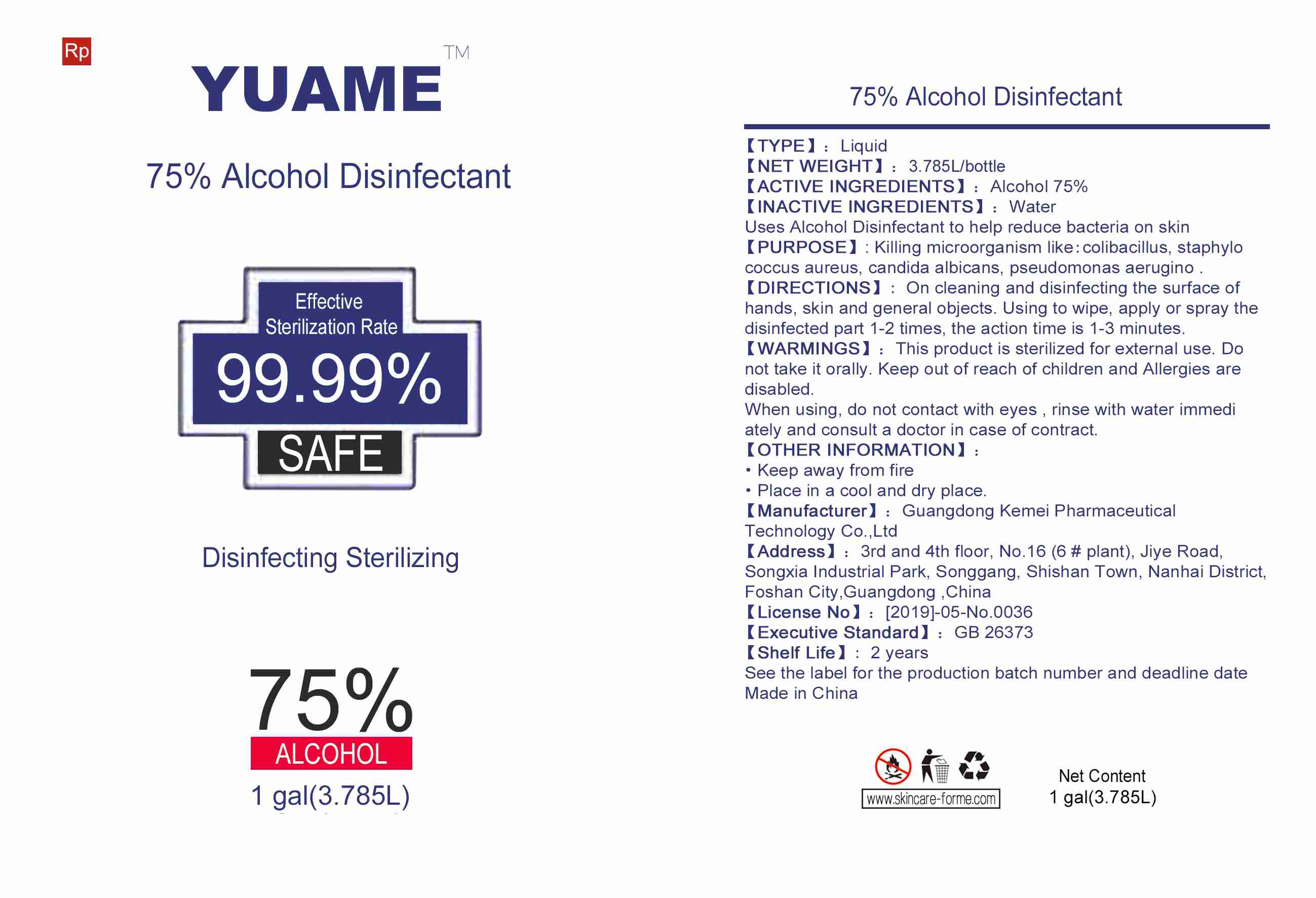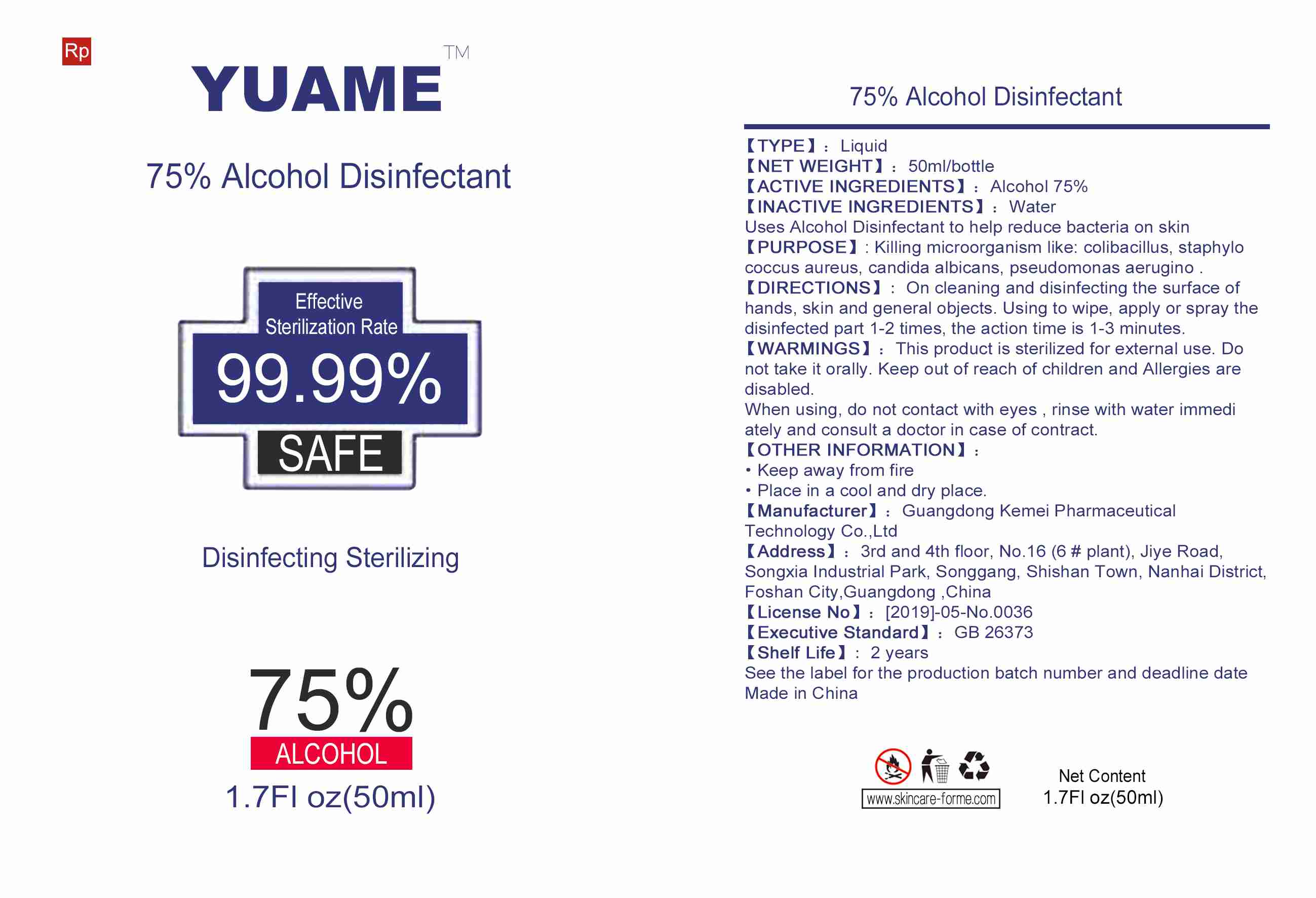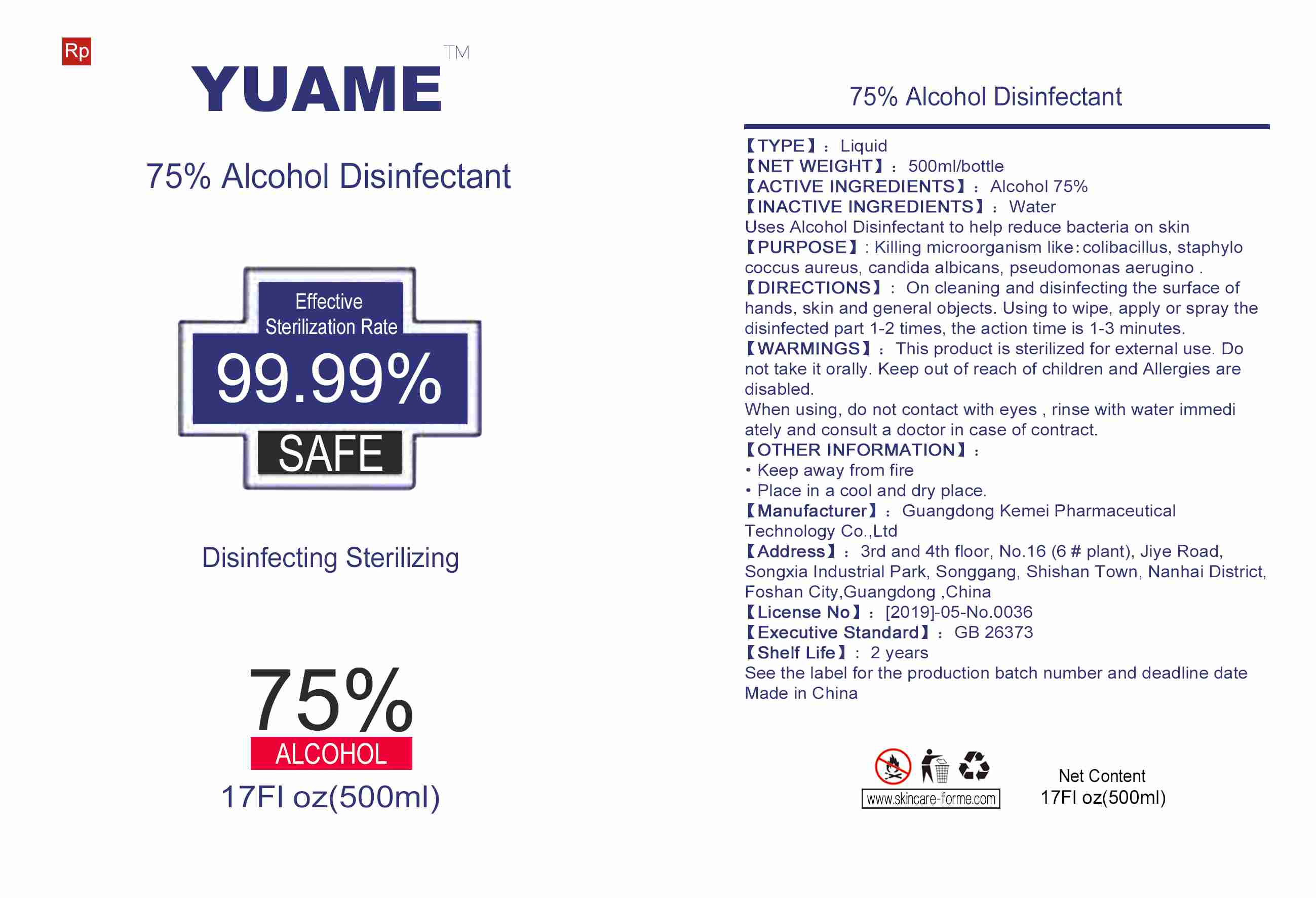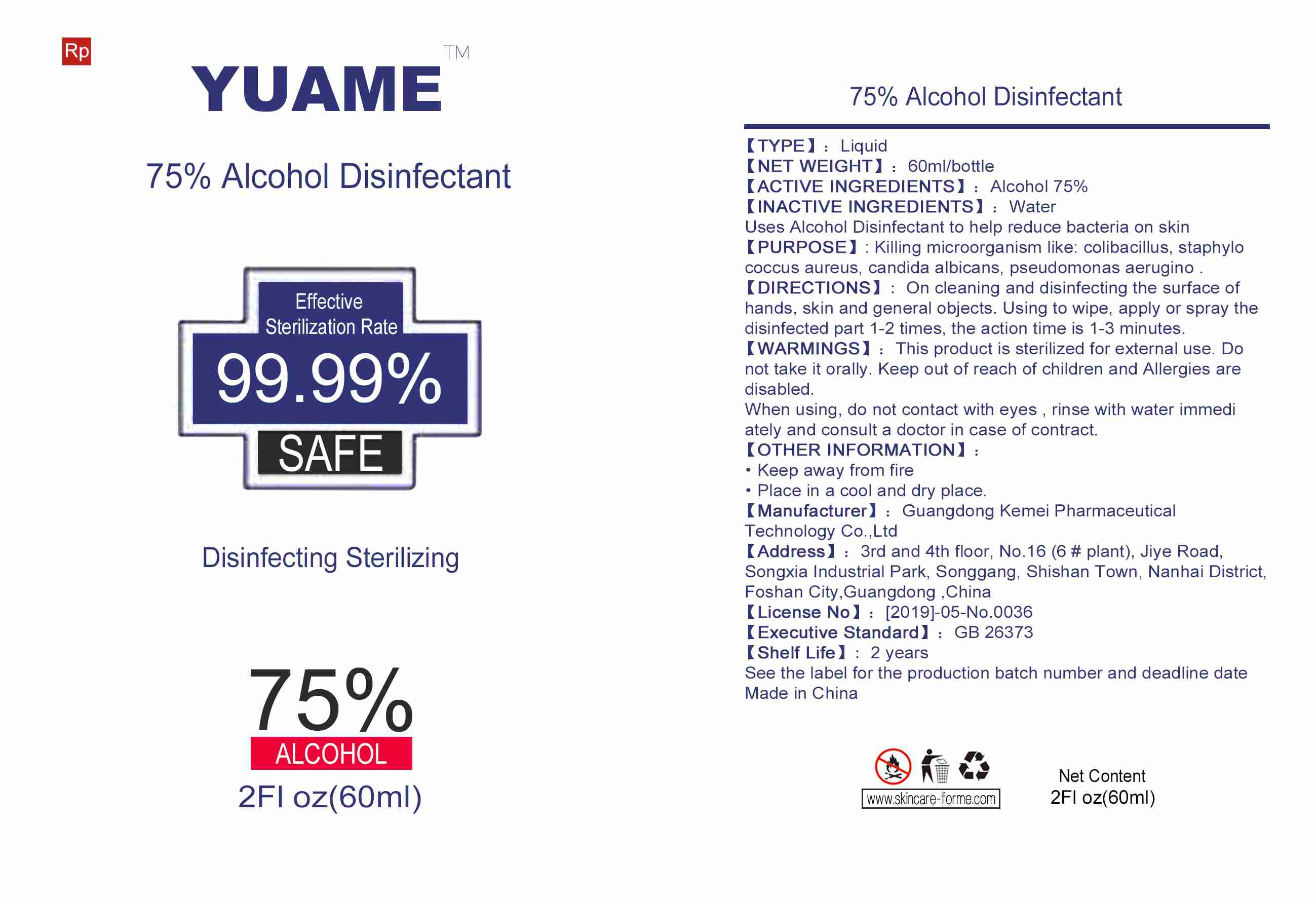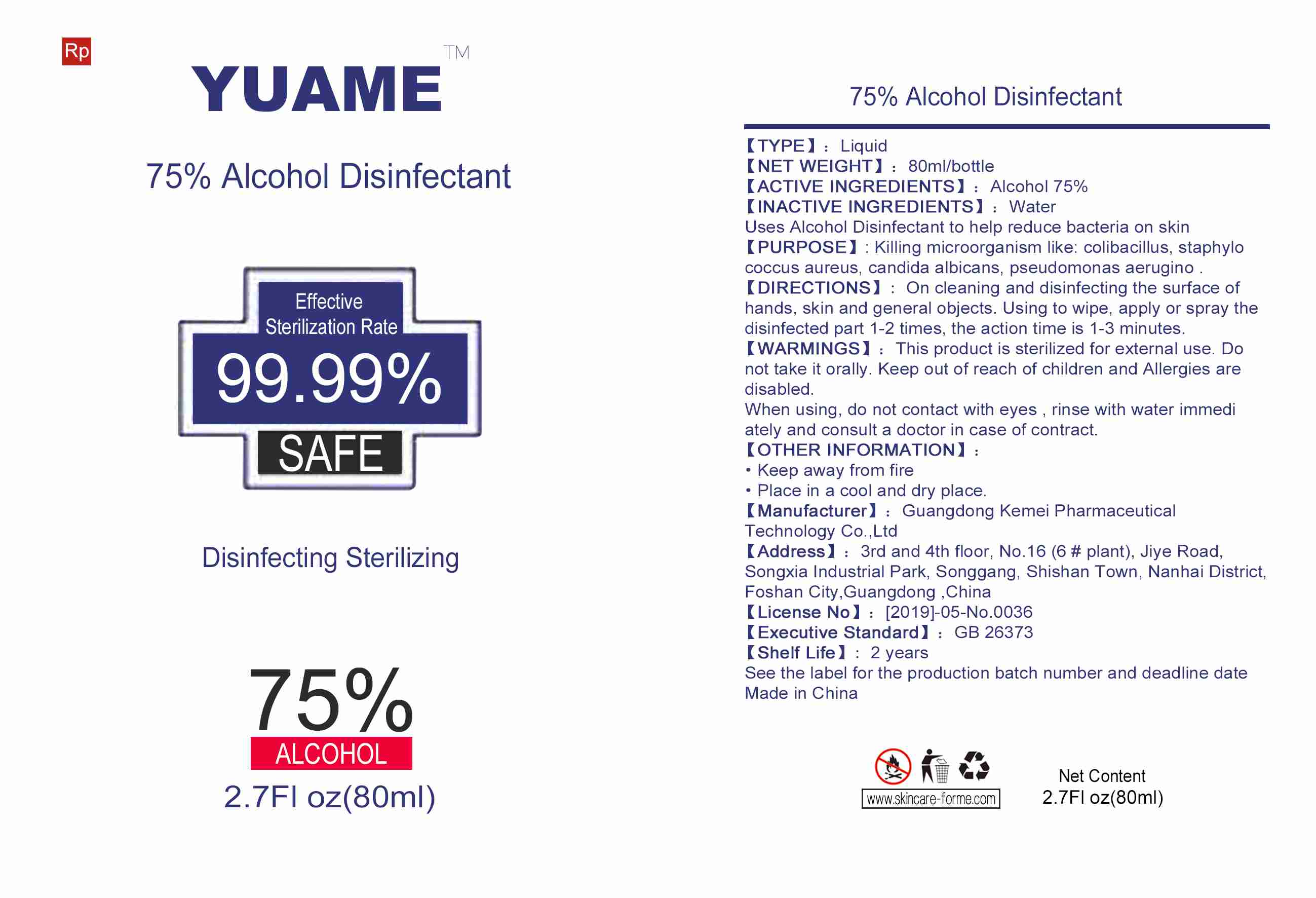 DRUG LABEL: 75% Alcohol Disinfectant
NDC: 75132-002 | Form: LIQUID
Manufacturer: Guangdong Kemei Pharmaceutical Technology Co., Ltd.
Category: otc | Type: HUMAN OTC DRUG LABEL
Date: 20200603

ACTIVE INGREDIENTS: ALCOHOL 75 mL/100 mL
INACTIVE INGREDIENTS: WATER

75% Alcohol Disinfectant

ACTIVE INGREDIENTS

Alcohol 75%

Purpose

Killing microorganism like colibacillus, staphylococcus aureus,candida albicans,

pseudomonas aerugino.

Uses

Uses Hand Sanitizer to help reduce bacteria on skin

Warnings

This product is sterilized for external use. Do not take it orally. Keep out of reach of children and Allergies are disabled.

Do not take it orally.

WHEN USING

When using, do not contact with eyes, rinse with water immediately and consult a doctor in case of contract.

STOP USE

/

Keep out of reach of children and Allergies are disabled.

Directions

On cleaning and disinfecting the surface of hands, skin

and general objects Using to wipe, apply or spray the

disinfected part 1-2 times, the action time is 1-3

minutes.

Other information

Keep away from fire
Place in a cool and dry place